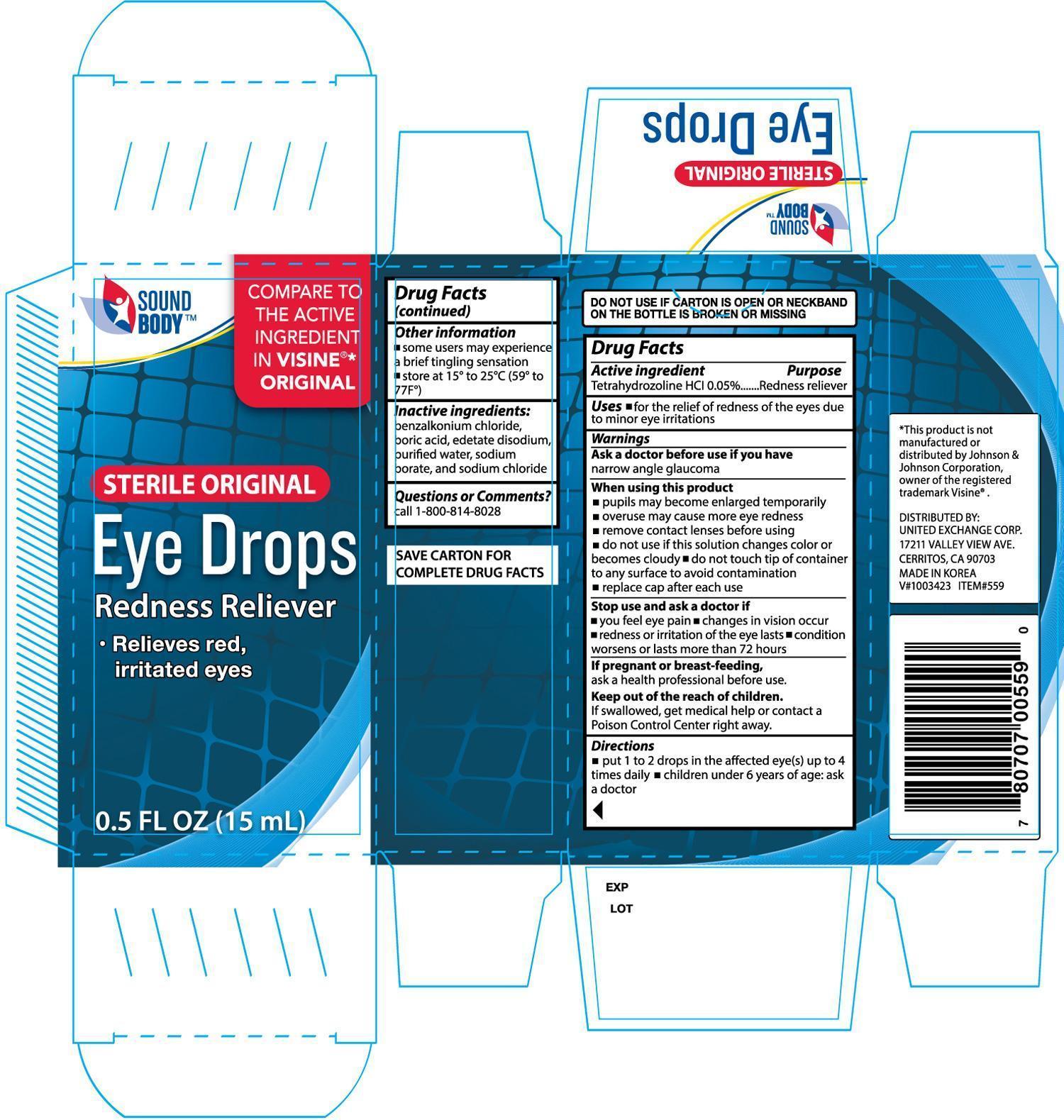 DRUG LABEL: Sound Body Original Eye
NDC: 65923-559 | Form: SOLUTION/ DROPS
Manufacturer: United Exchange Corp
Category: otc | Type: HUMAN OTC DRUG LABEL
Date: 20140519

ACTIVE INGREDIENTS: TETRAHYDROZOLINE HYDROCHLORIDE 0.5 mg/10 mg
INACTIVE INGREDIENTS: BENZALKONIUM CHLORIDE; BORIC ACID; EDETATE DISODIUM; WATER; SODIUM BORATE; SODIUM CHLORIDE

Drug Facts

Active ingredient Purpose

Tetrahydrozoline HCl 0.05% Redness Reliever

Uses

For the relief of redness of the eyes due to minor eye irritations

Warnings

Ask a doctor before use if you have

narrow angle glaucoma

When using this product

- pupils may become enlarged temporarily
- overuse may cause more eye redness
- remove contact lenses before using
- do not use if this solution changes color or becomes cloudy
- do not touch tip of container to any surface to avoid contamination
- replace cap after each use

Stop use and ask a doctor if

- you feel eye pain
- changes in vision occur
- redness or irritation of the eye lasts
- condition worsens or last more than 72 hours

If pregnant or breast-feeding,

ask a health professional before use

Keep out of the reach of children.

if swallowed, get medical help or contact a Poison Control Center right away.

Directions

- put 1 to 2 drops in the affected eye(s) up to 4 times daily
- children under 6 years of age: ask a doctor

Other information

- some users may experience a brief tingling sensation
- store at 15° to 25°C (59° to 77°F)

INACTIVE INGREDIENT

Inactive ingredients: benzalkonium chloride, boric acid, edetate disodium, purified water, sodium borate, and sodium chloride

DOSAGE AND ADMINISTRATION

Distributed By:

United Exchange Corp.

17211 Valley View Ave.

Cerritos, CA 90703

Made in Korea